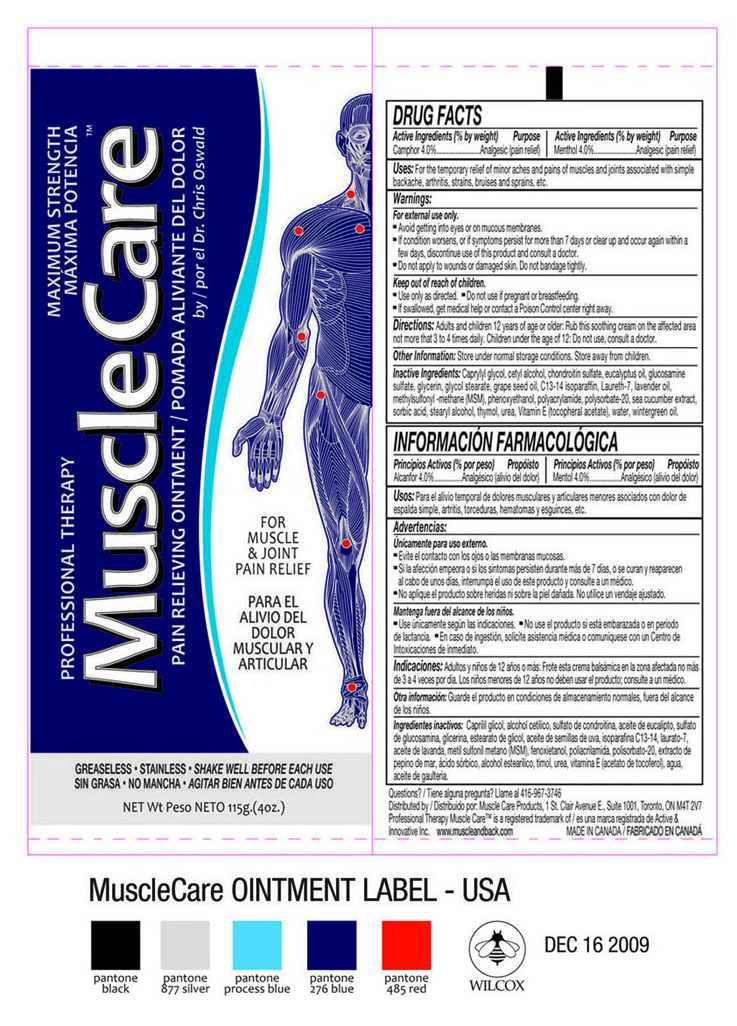 DRUG LABEL: Camphor, Menthol
NDC: 50421-004 | Form: OINTMENT
Manufacturer: Active & Innovative Inc.
Category: otc | Type: HUMAN OTC DRUG LABEL
Date: 20100113

ACTIVE INGREDIENTS: CAMPHOR 4.6 g/115 g; MENTHOL 4.6 g/115 g
INACTIVE INGREDIENTS: CAPRYLYL GLYCOL; CETYL ALCOHOL; EUCALYPTUS OIL; GLUCOSAMINE SULFATE; GLYCERIN; GLYCOL STEARATE; C13-14 ISOPARAFFIN; LAVENDER OIL; DIMETHYL SULFONE; PHENOXYETHANOL; POLYSORBATE 20; SORBIC ACID; STEARYL ALCOHOL; THYMOL; UREA; .ALPHA.-TOCOPHEROL ACETATE, DL-; WATER; METHYL SALICYLATE

DRUG FACTS

Active Ingredients (% by weight)

Camphor4.0%
Menthol 4.0%

Purpose

Analgesic (pain relief)

Uses

For the temporary relief of minor aches and pains of muscles and joints associated with simple backache, arthritis, strains, bruises and sprains, etc.

Warnings

- For external use only.
- Avoid getting into eyes or on mucous membranes.
- If the conditions worsens, or if the symptoms persists for more than 7 days or clears up and occurs again within a few days, discontinue use of this product and consult a doctor.
- Do not apply to wounds or damaged skin. Do not bandage tightly.

OTC - Keep Out of Reach of Children Section

Keep out of reach of children.

Other Warnings

- Use only as directed.
- Do not use if pregnant or breastfeeding.
- If swallowed, get medical help or contact a poison Control center right away.

Directions

Adults and children 12 years of age or older: Rub this soothing cream on the affected area not more that 3 to 4 times daily.
Children under the age of 12: Do not use, consult a doctor.

Other Information

Store under normal storage conditions. Store away from Children.

Inactive Ingredients

Caprylyl glycol, cetyl alcohol, chondroitin sulphate, eucalyptus oil, glucosamine sulfate, glycerin, glycol stearate, grape seed oil, C13-14 isoparaffin, Laureth-7, lavender oil, methylsulfonyl-methane (MSM), phenoxyethanol, polyacrylamide, polysorbate-20, sea cucumber extract, sorbic acid, stearyl alcohol, thymol, urea, Vitamin E (tocopheral acetate), water, wintergreen oil.

Questions?

Questions? 416-967-3746

Principal Display Panel

PROFESSIONAL THERAPY MAXIMUM STRENGTH
MAXIMA POTENCIA
MuscleCare TM
PAIN RELIEVING OINTMENT/ POMADA ALIVIANTE DEL DOLOR
by / por el Dr. Chris Oswald
FOR
MUSCLE
& JOINT
PAIN RELIEF
PARA EL
ALIVIO DEL
DOLOR
MUSCULAR Y
ARTICULAR
GREASELESS ● STAINLESS ● SHAKE WELL BEFORE EACH USE
SIN GRASA ● NO MANCHA ● AGITAR BIEN ANTES DE CADA USO
NET WT Peso NETO 115g. (4oz.)